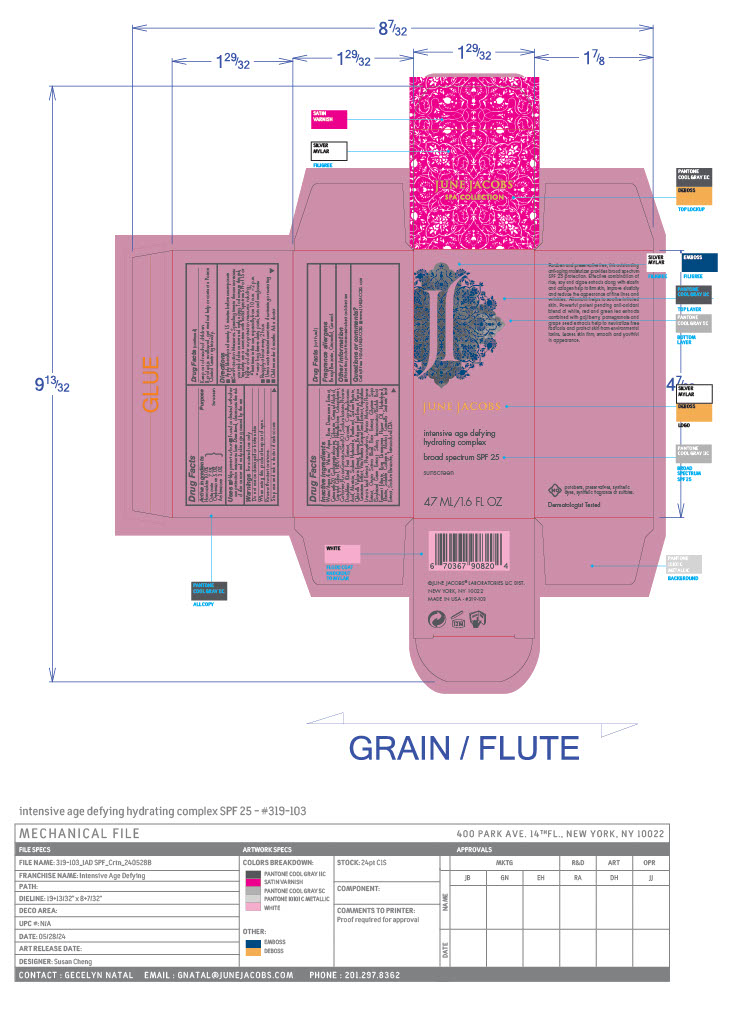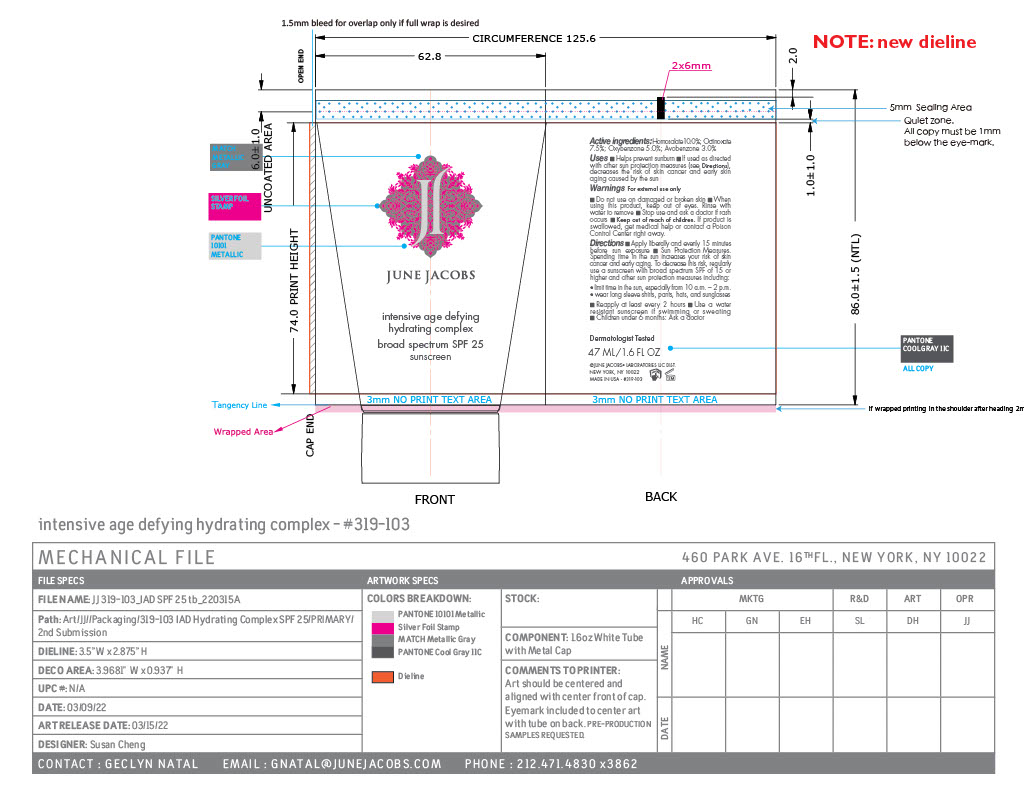 DRUG LABEL: Intensive Age Defying Hydrating Complex SPF 25
NDC: 65278-103 | Form: CREAM
Manufacturer: June Jacobs Labs, LLC
Category: otc | Type: HUMAN OTC DRUG LABEL
Date: 20240521

ACTIVE INGREDIENTS: OCTINOXATE 3.549 g/47.32 g; AVOBENZONE 1.4196 g/47.32 g; HOMOSALATE 4.732 g/47.32 g; OXYBENZONE 2.366 g/47.32 g
INACTIVE INGREDIENTS: PANTHENOL; ASPALATHUS LINEARIS LEAF; PHENOXYETHANOL; ARNICA MONTANA FLOWER; RICE BRAN; HYDROLYZED BOVINE ELASTIN (BASE; 1000 MW); HEXAMETHYLENE DIISOCYANATE/TRIMETHYLOL HEXYLLACTONE CROSSPOLYMER; PHYTATE SODIUM; CARBOMER HOMOPOLYMER, UNSPECIFIED TYPE; LYCIUM BARBARUM FRUIT; ROSA DAMASCENA FLOWER OIL; ALCOHOL; ROSA DAMASCENA FLOWERING TOP; POLYOXYL 20 CETOSTEARYL ETHER; CAPRYLYL GLYCOL; PUNICA GRANATUM SEED OIL; ALLANTOIN; CARAMEL; CAPRYLHYDROXAMIC ACID; EDETATE SODIUM; .BETA.-CITRONELLOL, (R)-; GERANIOL; CETOSTEARYL ALCOHOL; CHLORELLA VULGARIS; SILICON DIOXIDE; SODIUM BENZOATE; BENZYL BENZOATE; SODIUM HYDROXIDE; PUNICA GRANATUM ROOT BARK; VITIS VINIFERA SEED; SOYBEAN GERM; COLLAGEN, SOLUBLE, FISH SKIN; WATER; LEUCONOSTOC/RADISH ROOT FERMENT FILTRATE; GREEN TEA LEAF; CYCLOMETHICONE 5; GLYCERIN; SODIUM LACTATE, L-; DATE

Intensive Age Defying Hydrating Complex SPF 25

Active ingredients

Homosalate 10.0%

Octinoxate 7.5%

Oxybenzone 5.0%

Avobenzone 3.0%

PURPOSE

Sunscreen

INDICATIONS AND USAGE

Uses ■ Helps prevent sunburn ■ If used as directed with other sun protection measures (see Directions), decreases the risk of skin cancer and early skin aging caused by the sun

Warnings

For external use only

Do not use on damaged or broken skin

When using this product keep out of eyes.

Rinse with water to remove.

Stop use and ask a doctor if rash occurs

Keep out of reach of children. If product is swallowed, get medical help or contact a Poison Control Center right away.

DOSAGE AND ADMINISTRATION

Directions ■Sun Protection Measures. Spending time in the sun increases your risk of skin cancer and early aging. To decrease this risk, regularly use a sunscreen with broad spectrum SPF of 15 or higher and other sun protection measures including: • limit time in the sun, especially from 10 a.m. – 2 p.m. • wear long sleeve shirts, pants, hats and sunglasses

■ Reapply at least every 2 hours ■ Use a water resistant sunscreen if swimming or sweating ■ Children under 6 months: Ask a doctor

Inactive ingredients

Water/Aqua/Eau, Water/ Aqua, Rosa Damascena Extract, Ceteareth-20, Cyclopentasiloxane, Glycerin, Cetearyl Alcohol, Caprylyl Glycol, HDI/Trimethylol Hexyllactone Crosspolymer, Carbomer, Punica Granatum Seed Oil, Sodium Lactate, Phoenix Dactylifera (Date) Fruit Extract, Caramel, Caprylhydroxamic Acid, Allantoin, Sodium Hydroxide, Panthenol, Sodium Phytate, Chlorella Vulgaris Extract, Lycium Barbarum Fruit Extract, Punica Granatum Extract, Vitis Vinifera (Grape) Seed Extract, Aspalathus Linearis Leaf Extract, Phenoxyethano, Arnica Montana Flower Extract, Oryza Sativa (Rice) Bran Extract, Glycine Soja (Soybean) Germ Extract, Silica, Leuconostoc/Radish Root Ferment Filtrate, Rosa Damascena Flower Oil, Hydrolyzed Elastin, Soluble Collagen, Alcohol, Camellia Sinensis Leaf Extract, Sodium Benzoate, Tetrasodium EDTA, Benzyl Benzoate, Citronellol, Geraniol.

Other information ■ Protect this product from excessive heat and direct sun

Questions or comments? Call toll free 1-866-JUNEJACOBS ■ www.JUNEJACOBS.com